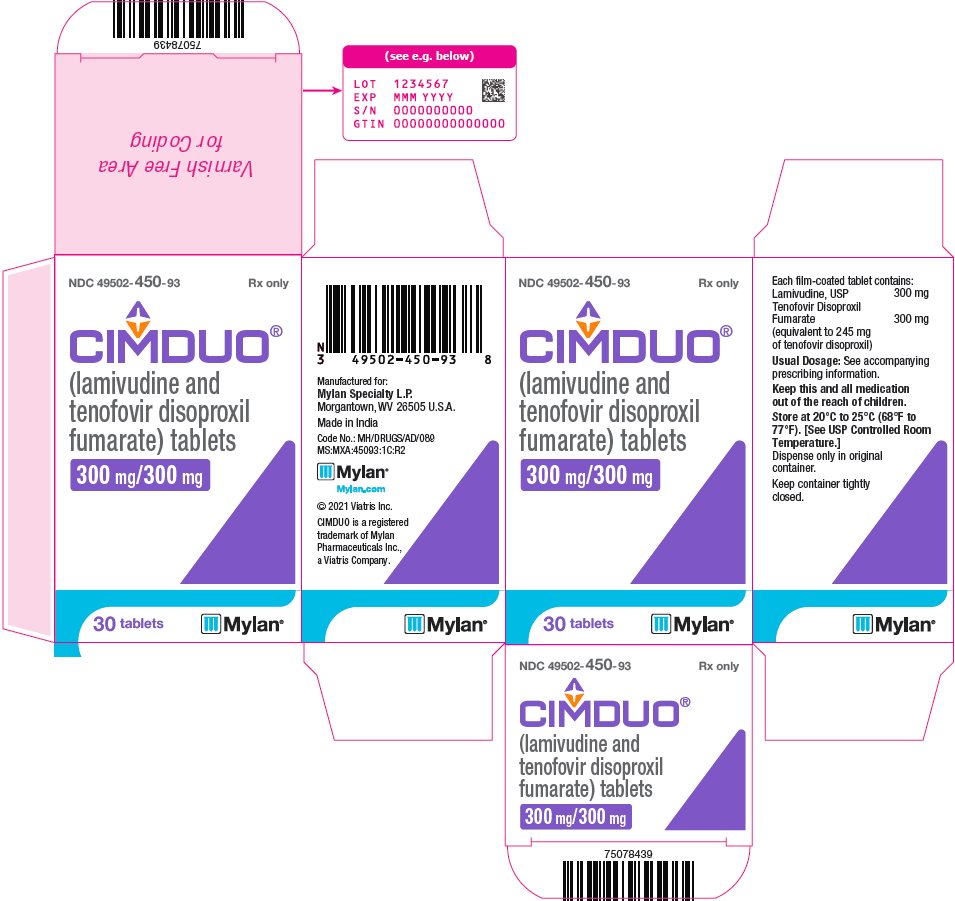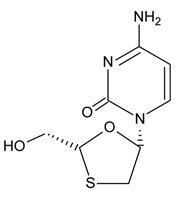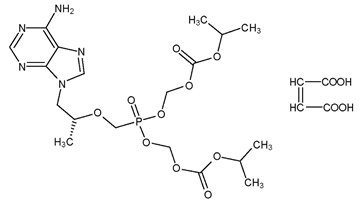 DRUG LABEL: CIMDUO
NDC: 49502-450 | Form: TABLET, FILM COATED
Manufacturer: Viatris Specialty LLC
Category: prescription | Type: HUMAN PRESCRIPTION DRUG LABEL
Date: 20210215

ACTIVE INGREDIENTS: LAMIVUDINE 300 mg/1 1; TENOFOVIR DISOPROXIL FUMARATE 300 mg/1 1
INACTIVE INGREDIENTS: CROSCARMELLOSE SODIUM; LACTOSE MONOHYDRATE; MAGNESIUM STEARATE; MICROCRYSTALLINE CELLULOSE; POLYETHYLENE GLYCOL, UNSPECIFIED; POLYVINYL ALCOHOL, UNSPECIFIED; TALC; TITANIUM DIOXIDE

HIGHLIGHTS OF PRESCRIBING INFORMATION

These highlights do not include all the information needed to use CIMDUO safely and effectively. See full prescribing information for CIMDUO.
CIMDUO® (lamivudine and tenofovir disoproxil fumarate) tablets, for oral use
Initial U.S. Approval: 2018

WARNING: POST TREATMENT ACUTE EXACERBATIONS OF HEPATITIS B

See full prescribing information for complete boxed warning.

- Severe acute exacerbations of hepatitis B have been reported in patients who are co-infected with HBV and human immunodeficiency virus (HIV-1) and have discontinued lamivudine and tenofovir disoproxil fumarate. Monitor hepatic function closely in these patients and, if appropriate, initiate anti-hepatitis B treatment. (5.2)

1 INDICATIONS AND USAGE

CIMDUO is a two-drug combination of lamivudine (3TC) and tenofovir disoproxil fumarate (TDF), both nucleo(t)side reverse transcriptase inhibitors and is indicated in combination with other antiretroviral agents for the treatment of human immunodeficiency virus type 1 (HIV-1) infection in adult and pediatric patients weighing at least 35 kg. (1)

2 DOSAGE AND ADMINISTRATION

- Testing: Prior to initiation and during treatment with CIMDUO, patients should be tested for hepatitis B virus infection, and estimated creatinine clearance, urine glucose, and urine protein should be obtained. (2.1)
- Recommended dose: One tablet taken orally once daily with or without food. (2.2)
- Renal Impairment: Not recommended in patients with CrCL less than 50 mL/min or patients with end-stage renal disease requiring hemodialysis. (2.3)

3 DOSAGE FORMS AND STRENGTHS

Tablets: 300 mg lamivudine and 300 mg tenofovir disoproxil fumarate (equivalent to 245 mg of tenofovir disoproxil). (3)

4 CONTRAINDICATIONS

- CIMDUO is contraindicated in patients with previous hypersensitivity to any of the components of this product. (4)

5 WARNINGS AND PRECAUTIONS

- Lactic Acidosis/Severe Hepatomegaly with Steatosis: Discontinue treatment in patients who develop symptoms or laboratory findings suggestive of lactic acidosis or pronounced hepatotoxicity. (5.1)
- New Onset or Worsening Renal Impairment: Can include acute renal failure and Fanconi syndrome. Assess estimated creatinine clearance before initiating treatment with tenofovir disoproxil fumarate, a component of CIMDUO. In patients at risk for renal dysfunction, assess estimated creatinine clearance, serum phosphorus, urine glucose and urine protein before initiating treatment with tenofovir and periodically during treatment. Avoid administering CIMDUO with concurrent or recent use of nephrotoxic drugs. (5.3)
- Hepatic decompensation, some fatal, has occurred in HIV-1/HCV co-infected patients receiving combination antiretroviral therapy and interferon- and ribavirin-based regimens. Monitor for treatment-associated toxicities. Discontinue CIMDUO, as medically appropriate, and consider dose reduction or discontinuation of interferon alfa, ribavirin, or both. (5.4)
- Pancreatitis: Use with caution in pediatric patients with a history of pancreatitis or other significant risk factors for pancreatitis. Discontinue CIMDUO as clinically appropriate. (5.5)
- Decreases in Bone Mineral Density (BMD): Observed in HIV-infected patients. Consider assessment of BMD in patients with a history of pathologic fracture or other risk factors for osteoporosis or bone loss. (5.6)
- Immune Reconstitution Syndrome: Observed in HIV-infected patients. May necessitate further evaluation and treatment. (5.7)
- Redistribution/Accumulation of Body Fat: Observed in HIV-infected patients receiving antiretroviral combination therapy. (5.8)
- Triple Nucleoside-Only Regimens: Early virologic failure has been reported in HIV-infected patients. Monitor carefully and consider treatment modification. (5.9)

6 ADVERSE REACTIONS

- Most common adverse reactions (> 10% with CIMDUO) are headache, pain, depression, diarrhea, and rash. (6)

To report SUSPECTED ADVERSE REACTIONS, contact Mylan at 1-877-446-3679 (1-877-4-INFO-RX) or FDA at 1-800-FDA-1088 or www.fda.gov/medwatch.

7 DRUG INTERACTIONS

- Atazanavir: Atazanavir should be coadministered with ritonavir when coadministered with CIMDUO. (7.2)
- HIV-1 Protease Inhibitors: Monitor for evidence of tenofovir toxicity when CIMDUO is coadministrated with atazanavir/ritonavir, darunavir/ritonavir, or lopinavir/ritonavir. (7.2)
- Sorbitol: Avoid chronic administration of sorbitol with CIMDUO.(7.5)

8 USE IN SPECIFIC POPULATIONS

- Lactation: Breastfeeding not recommended due to potential for HIV transmission. (8.2)

FULL PRESCRIBING INFORMATION

WARNING: POST TREATMENT ACUTE EXACERBATIONS OF HEPATITIS B

Severe acute exacerbations of hepatitis B have been reported in patients who are co-infected with hepatitis B virus (HBV) and human immunodeficiency virus (HIV-1) and have discontinued lamivudine or tenofovir disoproxil fumarate, components of CIMDUO. Monitor hepatic function closely in these patients and, if appropriate, initiate anti-hepatitis B treatment [see Warnings and Precautions (5.2)].

1 INDICATIONS AND USAGE

CIMDUO® (lamivudine and tenofovir disoproxil fumarate) is indicated in combination with other antiretroviral agents for the treatment of human immunodeficiency virus type 1 (HIV-1) infection in adult and pediatric patients weighing at least 35 kg.

2 DOSAGE AND ADMINISTRATION

2.1 Testing Prior to Initiation and During Treatment with CIMDUO

Prior to initiation of CIMDUO, test patients for hepatitis B virus infection [see Warnings and Precautions (5.2)].

It is recommended that serum creatinine, serum phosphorus, estimated creatinine clearance, urine glucose, and urine protein be assessed before initiating CIMDUO and during therapy in all patients as clinically appropriate [see Warnings and Precautions (5.3)].

2.2 Recommended Dosage for Adult and Pediatric Patients Weighing at Least 35 kg

CIMDUO is a two-drug fixed-dose combination product containing 300 mg of lamivudine (3TC) and 300 mg of tenofovir disoproxil fumarate (TDF). The recommended dosage of CIMDUO in HIV-1-infected adult and pediatric patients weighing at least 35 kg is one tablet taken orally once daily with or without food.

2.3 Not Recommended in Renal Impairment

Because CIMDUO is a fixed-dose combination tablet and cannot be dose adjusted, it is not recommended for patients with impaired renal function (creatinine clearance less than 50 mL/min) or patients with end-stage renal disease (ESRD) requiring hemodialysis [see Use in Specific Populations (8.6)].

3 DOSAGE FORMS AND STRENGTHS

Tablets: 300 mg of lamivudine and 300 mg of tenofovir disoproxil fumarate (equivalent to 245 mg of tenofovir disoproxil).

The tablets are white to off-white, film-coated, oval tablets debossed with “M112” on one side and plain on the other side.

4 CONTRAINDICATIONS

CIMDUO is contraindicated in patients with a previous hypersensitivity reaction to any of the components contained in the formulation.

5 WARNINGS AND PRECAUTIONS

5.1 Lactic Acidosis and Severe Hepatomegaly with Steatosis

Lactic acidosis and severe hepatomegaly with steatosis, including fatal cases, have been reported with the use of nucleoside analogs and other antiretrovirals. Treatment should be suspended in any patient who develops clinical or laboratory findings suggestive of lactic acidosis or pronounced hepatotoxicity (which may include hepatomegaly and steatosis even in the absence of marked transaminase elevations).

5.2 Severe Acute Exacerbation of Hepatitis B in Patients Coinfected with HIV-1 and HBV

Posttreatment Exacerbations of Hepatitis

All patients with HIV-1 should be tested for the presence of chronic hepatitis B virus (HBV) before initiating antiretroviral therapy. Discontinuation of anti-HBV therapy, including 3TC and TDF, may be associated with severe acute exacerbations of hepatitis. Patients infected with HBV who discontinue CIMDUO should be closely monitored with both clinical and laboratory follow-up for at least several months after stopping treatment. If appropriate, resumption of anti-hepatitis B therapy may be warranted.

Important Differences Among Lamivudine-Containing Products

CIMDUO tablets contain a higher dose of the same active ingredient, 3TC, than EPIVIR-HBV® tablets. EPIVIR-HBV was developed for patients with chronic hepatitis B. The formulation and dosage of 3TC in EPIVIR-HBV are not appropriate for patients co-infected with HIV-1 and HBV. Safety and efficacy of 3TC have not been established for treatment of chronic hepatitis B in patients co-infected with HIV-1 and HBV.

If treatment with EPIVIR-HBV, TDF, or a tenofovir alafenamide (TAF)-containing product is prescribed for chronic hepatitis B for a patient with unrecognized or untreated HIV-1 infection, rapid emergence of HIV-1 resistance is likely to result because of the subtherapeutic dose and the inappropriateness of monotherapy HIV-1 treatment.

5.3 New Onset or Worsening Renal Impairment

TDF, a component of CIMDUO is principally eliminated by the kidney. Renal impairment, including cases of acute renal failure and Fanconi syndrome (renal tubular injury with severe hypophosphatemia), has been reported with the use of TDF [see Adverse Reactions (6.2)].

It is recommended that estimated creatinine clearance be assessed in all patients prior to initiating therapy and as clinically appropriate during therapy with TDF. In patients at risk of renal dysfunction, it is recommended that estimated creatinine clearance, serum phosphorus, urine glucose, and urine protein be assessed prior to initiation of tenofovir disoproxil fumarate, and periodically during TDF therapy.

Avoid CIMDUO with concurrent or recent use of a nephrotoxic agent (e.g., high-dose or multiple non-steroidal anti-inflammatory drugs (NSAIDs)) [see Drug Interactions (7.1)]. Cases of acute renal failure after initiation of high dose or multiple NSAIDs have been reported in HIV-infected patients with risk factors for renal dysfunction who appeared stable on TDF. Some patients required hospitalization and renal replacement therapy. Alternatives to NSAIDs should be considered, if needed, in patients at risk for renal dysfunction.

Persistent or worsening bone pain, pain in extremities, fractures and/or muscular pain or weakness may be manifestations of proximal renal tubulopathy and should prompt an evaluation of renal function in at-risk patients.

5.4 Risk of Hepatic Decompensation When Used with Interferon- and Ribavirin-Based Regimens

In vitro studies have shown ribavirin can reduce the phosphorylation of pyrimidine nucleoside analogues such as 3TC, a component of CIMDUO. Although no evidence of a pharmacokinetic or pharmacodynamic interaction (e.g., loss of HIV-1/HCV virologic suppression) was seen when ribavirin was coadministered with 3TC in HIV-1/HCV co-infected patients [see Clinical Pharmacology (12.3)], hepatic decompensation (some fatal) has occurred in HIV-1/HCV co-infected patients receiving combination antiretroviral therapy for HIV-1 and interferon alfa with or without ribavirin. Patients receiving interferon alfa with or without ribavirin and 3TC should be closely monitored for treatment-associated toxicities, especially hepatic decompensation. Discontinuation of 3TC should be considered as medically appropriate. Dose reduction or discontinuation of interferon alfa, ribavirin, or both should also be considered if worsening clinical toxicities are observed, including hepatic decompensation (e.g., Child-Pugh > 6). See the full prescribing information for interferon and ribavirin.

5.5 Pancreatitis

In pediatric patients with a history of prior antiretroviral nucleoside exposure, a history of pancreatitis, or other significant risk factors for the development of pancreatitis, 3TC, a component of CIMDUO, should be used with caution. Treatment with CIMDUO should be stopped immediately if clinical signs, symptoms, or laboratory abnormalities suggestive of pancreatitis occur [see Adverse Reactions (6.1)].

5.6 Bone Effects

Bone Mineral Density (BMD)

In clinical trials in HIV-1-infected adults, TDF was associated with slightly greater decreases in BMD and increases in biochemical markers of bone metabolism, suggesting increased bone turnover relative to comparators. Serum parathyroid hormone levels and 1,25 Vitamin D levels were also higher in subjects receiving TDF [see Adverse Reactions (6.1)].

The effects of TDF-associated changes in BMD and biochemical markers on long-term bone health and future fracture risk are unknown. Assessment of BMD should be considered for adults who have a history of pathologic bone fracture or other risk factors for osteoporosis or bone loss. Although the effect of supplementation with calcium and vitamin D was not studied, such supplementation may be beneficial for all patients. If bone abnormalities are suspected then appropriate consultation should be obtained.

Mineralization Defects

Cases of osteomalacia associated with proximal renal tubulopathy, manifested as bone pain or pain in extremities and which may contribute to fractures, have been reported in association with the use of TDF [see Adverse Reactions (6.2)]. Arthralgias and muscle pain or weakness have also been reported in cases of proximal renal tubulopathy. Hypophosphatemia and osteomalacia secondary to proximal renal tubulopathy should be considered in patients at risk of renal dysfunction who present with persistent or worsening bone or muscle symptoms while receiving products containing TDF [see Warnings and Precautions (5.3)].

5.7 Immune Reconstitution Syndrome

Immune reconstitution syndrome has been reported in HIV-infected patients treated with combination antiretroviral therapy, including 3TC and TDF. During the initial phase of combination antiretroviral treatment, patients whose immune system responds may develop an inflammatory response to indolent or residual opportunistic infections (such as Mycobacterium avium infection, cytomegalovirus, Pneumocystis jirovecii pneumonia [PCP], or tuberculosis), which may necessitate further evaluation and treatment.

Autoimmune disorders (such as Graves’ disease, polymyositis, and Guillain-Barre syndrome) have also been reported to occur in the setting of immune reconstitution; however, the time to onset is more variable, and can occur many months after initiation of treatment.

5.8 Fat Redistribution

In HIV-infected patients, redistribution/accumulation of body fat including central obesity, dorsocervical fat enlargement (buffalo hump), peripheral wasting, facial wasting, breast enlargement, and “cushingoid appearance” have been observed in patients receiving combination antiretroviral therapy. The mechanism and long-term consequences of these events are currently unknown. A causal relationship has not been established.

5.9 Early Virologic Failure

Clinical trials in HIV-infected subjects have demonstrated that certain regimens that only contain three nucleoside reverse transcriptase inhibitors (NRTI) are generally less effective than triple drug regimens containing two NRTIs in combination with either a non-nucleoside reverse transcriptase inhibitor or a HIV-1 protease inhibitor. In particular, early virological failure and high rates of resistance substitutions have been reported. Triple nucleoside regimens should therefore be used with caution. Patients on a therapy utilizing a triple nucleoside-only regimen should be carefully monitored and considered for treatment modification.

6 ADVERSE REACTIONS

The following adverse reactions are discussed in other sections of the labeling:

- Lactic Acidosis/Severe Hepatomegaly with Steatosis [see Warnings and Precautions (5.1)].
- Exacerbations of Hepatitis B [see Boxed Warning, Warnings and Precautions (5.2)].
- New Onset or Worsening Renal Impairment [see Warnings and Precautions (5.3)].
- Hepatic Decompensation in Patients Co-infected with HIV-1 and Hepatitis C [see Warnings and Precautions (5.4)].
- Pancreatitis [see Warnings and Precautions (5.5)].
- Decreases in Bone Mineral Density [see Warnings and Precautions (5.6)].
- Immune Reconstitution Syndrome [see Warnings and Precautions (5.7)].
- Fat Redistribution [see Warnings and Precautions (5.8)].

6.1 Clinical Trials Experience

Because clinical studies are conducted under widely varying conditions, the adverse reaction rates observed in clinical trials of a drug cannot be directly compared to rates in the clinical trials of another drug and may not reflect the rates observed in practice.

Lamivudine and Tenofovir Disoproxil Fumarate

Study 903 - Adverse Reactions

The most common adverse reactions seen in a double-blind comparative controlled study in which 600 treatment-naïve subjects received TDF (N = 299) or stavudine (d4T) (N = 301) in combination with 3TC and EFV for 144 weeks were mild to moderate gastrointestinal events and dizziness.

Mild adverse reactions (Grade 1) were common with a similar incidence in both arms, and included dizziness, diarrhea, and nausea. Selected moderate to severe adverse reactions are summarized in Table 1.

Table 1. Selected Adverse Reactions [Frequencies of adverse reactions are based on all treatment-emergent adverse events, regardless of relationship to study drug.] (Grades 2-4) Reported in ≥ 5% in Any Treatment Group in Study 903 (0-144 Weeks)
 | TDF + 3TC + EFV | d4T + 3TC + EFV
 | N = 299 | N = 301
Body as a Whole
Headache | 14% | 17%
Pain | 13% | 12%
Fever | 8% | 7%
Abdominal pain | 7% | 12%
Back pain | 9% | 8%
Asthenia | 6% | 7%
Digestive System
Diarrhea | 11% | 13%
Nausea | 8% | 9%
Dyspepsia | 4% | 5%
Vomiting | 5% | 9%
Metabolic Disorders
Lipodystrophy [Lipodystrophy represents a variety of investigator-described adverse events not a protocol-defined syndrome.] | 1% | 8%
Musculoskeletal
Arthralgia | 5% | 7%
Myalgia | 3% | 5%
Nervous System
Depression | 11% | 10%
Insomnia | 5% | 8%
Dizziness | 3% | 6%
Peripheral neuropathy [Peripheral neuropathy includes peripheral neuritis and neuropathy.] | 1% | 5%
Anxiety | 6% | 6%
Respiratory
Pneumonia | 5% | 5%
Skin and Appendages
Rash event [Rash event includes rash, pruritus, maculopapular rash, urticaria, vesiculobullous rash, and pustular rash.] | 18% | 12%

Laboratory Abnormalities

With the exception of fasting cholesterol and fasting triglyceride elevations that were more common in the stavudine group (40% and 9%) compared with TDF (19% and 1%) respectively, laboratory abnormalities observed in this study occurred with similar frequency in the tenofovir disoproxil fumarate and stavudine treatment arms. A summary of Grade 3 and 4 laboratory abnormalities is provided in Table 2.

Table 2. Grade 3/4 Laboratory Abnormalities Reported in ≥ 1% of Tenofovir Disoproxil Fumarate Treated Subjects in Study 903 (0-144 Weeks)
 | TDF + 3TC + EFV | d4T + 3TC + EFV
 | N = 299 | N = 301
Any ≥ Grade 3 Laboratory Abnormality | 36% | 42%
Fasting Cholesterol (> 240 mg/dL) | 19% | 40%
Creatine Kinase (M: > 990 U/L; F: > 845 U/L) | 12% | 12%
Serum Amylase (> 175 U/L) | 9% | 8%
AST (M: > 180 U/L; F: > 170 U/L) | 5% | 7%
ALT (M: > 215 U/L; F: > 170 U/L) | 4% | 5%
Hematuria (> 100 RBC/HPF) | 7% | 7%
Neutrophils (< 750/mm^3) | 3% | 1%
Fasting Triglycerides (> 750 mg/dL) | 1% | 9%

Pancreatitis

Pancreatitis, which has been fatal in some cases, has been observed in antiretroviral nucleoside-experienced pediatric subjects receiving 3TC alone or in combination with other antiretroviral agents [see Warnings and Precautions (5.5)].

Changes in Bone Mineral Density

In HIV-1-infected adult subjects in Study 903, there was a significantly greater mean percentage decrease from baseline in BMD at the lumbar spine in subjects receiving TDF + 3TC + EFV (-2.2% ± 3.9) compared with subjects receiving d4T + 3TC + EFV (-1.0% ± 4.6) through 144 weeks. Changes in BMD at the hip were similar between the two treatment groups (-2.8% ± 3.5 in the TDF group vs. -2.4% ± 4.5 in the d4T group). In both groups, the majority of the reduction in BMD occurred in the first 24-48 weeks of the trial and this reduction was sustained through Week 144. Twenty-eight percent of TDF-treated subjects vs. 21% of the d4T-treated subjects lost at least 5% of BMD at the spine or 7% of BMD at the hip. Clinically relevant fractures (excluding fingers and toes) were reported in 4 subjects in the TDF group and 6 subjects in the d4T group. In addition, there were significant increases in biochemical markers of bone metabolism (serum bone-specific alkaline phosphatase, serum osteocalcin, serum C telopeptide, and urinary N telopeptide) and higher serum parathyroid hormone levels and 1,25 Vitamin D levels in the TDF group relative to the d4T group; however, except for bone-specific alkaline phosphatase, these changes resulted in values that remained within the normal range [see Warnings and Precautions (5.6)].

6.2 Postmarketing Experience

The following adverse reactions have been identified during post-approval use for each of the individual components of CIMDUO (3TC and TDF). Because these reactions are reported voluntarily from a population of unknown size, it is not always possible to reliably estimate their frequency or establish causal relationship to drug exposure. These reactions have been chosen for inclusion due to a combination of their seriousness, frequency of reporting, or potential causal connection to 3TC and TDF.

Lamivudine

Body as a Whole: redistribution/accumulation of body fat [see Warnings and Precautions (5.8)].

Endocrine and Metabolic: hyperglycemia.

General: weakness.

Hemic and Lymphatic: anemia (including pure red cell aplasia and severe anemias progressing on therapy).

Hepatic and Pancreatic: lactic acidosis and hepatic steatosis, posttreatment exacerbation of hepatitis B [see Boxed Warning, Warnings and Precautions (5.1, 5.2)].

Hypersensitivity: anaphylaxis, urticaria.

Musculoskeletal: muscle weakness, CPK elevation, rhabdomyolysis.

Skin: Alopecia, pruritus.

Tenofovir Disoproxil Fumarate

Immune System Disorders: allergic reaction, including angioedema.

Metabolism and Nutrition Disorders: lactic acidosis, hypokalemia, hypophosphatemia.

Respiratory, Thoracic, and Mediastinal Disorders: dyspnea.

Gastrointestinal Disorders: pancreatitis, increased amylase, abdominal pain.

Renal and Urinary Disorders: renal insufficiency, acute renal failure, renal failure, acute tubular necrosis, Fanconi syndrome, proximal renal tubulopathy, interstitial nephritis (including acute cases), nephrogenic diabetes insipidus, renal insufficiency, increased creatinine, proteinuria, polyuria [see Warnings and Precautions (5.3)].

Hepatobiliary Disorders: hepatic steatosis, hepatitis, increased liver enzymes (most commonly AST, ALT gamma GT).

Skin and Subcutaneous Tissue Disorders: rash.

Musculoskeletal and Connective Tissue Disorders: rhabdomyolysis, osteomalacia (manifested as bone pain and which may contribute to fractures), muscular weakness, myopathy.

General Disorders and Administration Site Conditions: asthenia.

The following adverse reactions, listed under the body system headings above, may occur as a consequence of proximal renal tubulopathy: rhabdomyolysis, osteomalacia, hypokalemia, muscular weakness, myopathy, hypophosphatemia.

7 DRUG INTERACTIONS

7.1 Drugs Affecting Renal Function

Since tenofovir is primarily eliminated by the kidneys [see Clinical Pharmacology (12.3)], coadministration of CIMDUO with drugs that reduce renal function or compete for active tubular secretion may increase serum concentrations of tenofovir and/or increase the concentrations of other renally eliminated drugs. Some examples include, but are not limited to cidofovir, acyclovir, valacyclovir, ganciclovir, valganciclovir, aminoglycosides (e.g., gentamicin), and high-dose or multiple NSAIDs [see Warnings and Precautions (5.3)].

7.2 HIV-1 Protease Inhibitors

TDF decreases the AUC and Cmin of atazanavir [see Clinical Pharmacology (12.3)]. When coadministered with CIMDUO, it is recommended that atazanavir 300 mg is given with ritonavir 100 mg. TDF should not be coadministered with atazanavir without ritonavir.

Lopinavir/ritonavir, atazanavir coadministered with ritonavir, and darunavir coadministered with ritonavir have been shown to increase tenofovir concentrations [see Clinical Pharmacology (12.3)]. Patients receiving CIMDUO concomitantly with lopinavir/ritonavir, atazanavir and ritonavir, or darunavir and ritonavir should be monitored for tenofovir-associated adverse reactions. CIMDUO should be discontinued in patients who develop tenofovir-associated adverse reactions.

7.3 Hepatitis C Antiviral Agents

Coadministration of TDF, a component of CIMDUO, and EPCLUSA® (sofosbuvir/velpatasvir) or HARVONI® (ledipasvir/sofosbuvir) has been shown to increase tenofovir exposure [see Clinical Pharmacology (12.3)].

In patients receiving TDF concomitantly with sofosbuvir/velpatasvir, monitor for adverse reactions associated with TDF.

In patients receiving CIMDUO concomitantly with ledipasvir/sofosbuvir without an HIV-1 protease inhibitor/ritonavir or an HIV-1 protease inhibitor/cobicistat combination, monitor for adverse reactions associated with tenofovir.

In patients receiving CIMDUO concomitantly with ledipasvir/sofosbuvir and an HIV-1 protease inhibitor/ritonavir or an HIV-1 protease inhibitor/cobicistat combination, consider an alternative HCV or antiretroviral therapy, as the safety of increased tenofovir concentrations in this setting has not been established. If coadministration is necessary, monitor for adverse reactions associated with tenofovir.

7.4 Drugs Inhibiting Organic Cation Transporters

3TC, a component of CIMDUO, is predominantly eliminated in the urine by active organic cationic secretion. The possibility of interactions with other drugs administered concurrently should be considered, particularly when their main route of elimination is active renal secretion via the organic cationic transport system (e.g., trimethoprim) [see Clinical Pharmacology (12.3)]. No data are available regarding interactions with other drugs that have renal clearance mechanisms similar to that of 3TC.

7.5 Sorbitol

Coadministration of single doses of 3TC and sorbitol resulted in a sorbitol dose-dependent reduction in 3TC exposures. When possible, avoid use of sorbitol-containing medicines with 3TC [see Clinical Pharmacology (12.3)].

8 USE IN SPECIFIC POPULATIONS

8.1 Pregnancy

Pregnancy Exposure Registry

There is a pregnancy exposure registry that monitors pregnancy outcomes in women exposed to CIMDUO during pregnancy. Healthcare providers are encouraged to register patients by calling the Antiretroviral Pregnancy Registry (APR) at 1-800-258-4263.

Risk Summary

Available data from the APR show no difference in the risk of overall major birth defects for 3TC compared to the background rate for major birth defects of 2.7% in the U.S. reference population of the Metropolitan Atlanta Congenital Defects Program (MACDP) (see Data).

3TC produced embryonic toxicity in rabbits at a dose that produced similar human exposures as the recommended clinical dose. The relevance of animal findings to human pregnancy registry data is not known. There are no adequate and well-controlled studies with TDF in pregnant women. Because animal reproduction studies are not always predictive of human response, TDF should be used during pregnancy only if clearly needed.

Human Data

Lamivudine

Based on prospective reports from the APR of over 11,000 exposures to 3TC during pregnancy resulting in live births (including over 4,300 exposed in the first trimester), there was no difference between 3TC and overall birth defects compared with the background birth defect rate of 2.7% in the U.S. reference population of the MACDP. The prevalence of defects in the first trimester was 3.1% (95% CI: 2.6% to 3.7%).

3TC pharmacokinetics were studied in pregnant women during 2 clinical trials conducted in South Africa. The trials assessed pharmacokinetics in 16 women at 36 weeks gestation using 150 mg 3TC twice daily with zidovudine, 10 women at 38 weeks gestation using 150 mg 3TC twice daily with zidovudine, and 10 women at 38 weeks gestation using 3TC 300 mg twice daily without other antiretrovirals. These trials were not designed or powered to provide efficacy information.

3TC pharmacokinetics in pregnant women were similar to those seen in non-pregnant adults and in postpartum women. 3TC concentrations were generally similar in maternal, neonatal, and umbilical cord serum samples. In a subset of subjects, amniotic fluid specimens were collected following natural rupture of membranes and confirmed that lamivudine crosses the placenta in humans. Amniotic fluid concentrations of lamivudine were typically 2 times greater than maternal serum levels and ranged from 1.2 to 2.5 mcg per mL (150 mg twice daily) and 2.1 to 5.2 mcg per mL (300 mg twice daily).

Animal Data

Lamivudine

Studies in pregnant rats showed that 3TC is transferred to the fetus through the placenta. Reproduction studies with orally administered 3TC have been performed in rats and rabbits at doses producing plasma levels up to approximately 35 times that for the recommended adult HIV dose. No evidence of teratogenicity due to 3TC was observed. Evidence of embryo-lethality was seen in the rabbit at exposure levels similar to those observed in humans but there was no indication of this effect in the rat at exposure levels up to 35 times those in humans.

Tenofovir Disoproxil Fumarate

Reproduction studies have been performed in rats and rabbits at doses up to 14 and 19 times the human dose based on body surface area comparisons and revealed no evidence of impaired fertility or harm to the fetus due to tenofovir.

8.2 Lactation

The Centers for Disease Control and Prevention recommend that HIV-1-infected mothers not breastfeed their infants to avoid risking postnatal transmission of HIV-1 infection.

Lamivudine

3TC is excreted into human milk. Samples of breast milk obtained from 20 mothers receiving 3TC monotherapy, 300 mg twice daily (2 times the dose in CIMDUO), had measurable concentrations of 3TC. There is no information on the effects of 3TC on the breastfed infant, or the effects of 3TC on milk production.

Tenofovir Disoproxil Fumarate

Samples of breast milk obtained from five HIV-1-infected mothers in the first postpartum week show that tenofovir is excreted in human milk at low levels. The impact of this exposure in breastfed infants is unknown and the effects of TDF on milk production is unknown.

Because of the potential for 1) HIV transmission (in HIV-negative infants); 2) developing viral resistance (in HIV-positive infants); and 3) adverse reactions in a breastfed infant similar to those seen in adults, instruct mothers not to breastfeed if they are receiving CIMDUO.

8.4 Pediatric Use

The safety and effectiveness of CIMDUO as a fixed-dose tablet in pediatric patients infected with HIV-1 and weighing at least 35 kg have been established based on clinical studies using the individual components (lamivudine and tenofovir disoproxil fumarate).

8.5 Geriatric Use

Clinical studies of CIMDUO did not include sufficient numbers of subjects aged 65 and over to determine whether they respond differently from younger subjects. In general, caution should be exercised in the administration of CIMDUO in elderly patients reflecting the greater frequency of decreased hepatic, renal, or cardiac function, and of concomitant disease or other drug therapy.

8.6 Renal Impairment

CIMDUO is not recommended for patients with impaired renal function (i.e., creatinine clearance less than 50 mL/min) or patients with end-stage renal disease (ESRD) requiring hemodialysis because it is a fixed-dose combination formulation that cannot be adjusted [see Dosage and Administration (2.3)].

10 OVERDOSAGE

If overdose occurs the patient must be monitored for evidence of toxicity, and standard supportive treatment applied as necessary.

Lamivudine: There is no known specific treatment for overdose with 3TC. If overdose occurs, the patient should be monitored and standard supportive treatment applied as required because a negligible amount of 3TC was removed via (4-hour) hemodialysis, continuous ambulatory peritoneal dialysis, and automated peritoneal dialysis, it is not known if continuous hemodialysis would provide clinical benefit in a 3TC overdose event.

Tenofovir Disoproxil Fumarate: Limited clinical experience at doses higher than the therapeutic dose of TDF 300 mg is available.

Tenofovir is efficiently removed by hemodialysis with an extraction coefficient of approximately 54%. Following a single 300-mg dose of tenofovir disoproxil fumarate, a 4-hour hemodialysis session removed approximately 10% of the administered tenofovir dose.

11 DESCRIPTION

CIMDUO tablets contain lamivudine (also known as 3TC), a synthetic nucleoside analogue with activity against HIV-1 and tenofovir disoproxil fumarate or tenofovir DF, a fumaric acid salt of bis-isopropoxycarbonyloxymethyl ester prodrug of tenofovir. In vivo tenofovir DF is converted to tenofovir, an acyclic nucleoside phosphonate (nucleotide) analog of adenosine 5’-monophosphate. Tenofovir exhibits activity against HIV-1 reverse transcriptase.

The chemical name of lamivudine is (-)-1-[2R,5S)-2-Hydroxymethyl)-1,3-oxathiolan-5-yl]cytosine. Lamivudine is the (-)enantiomer of a dideoxy analogue of cytidine. Lamivudine has also been referred to as (-)2′,3′-dideoxy, 3′-thiacytidine. It has a molecular formula of C8H11N3O3S and a molecular weight of 229.26 g per mol. It has the following structural formula:

Lamivudine is a white to off-white solid with a solubility of approximately 70 mg per mL in water at 20°C.

The chemical name of tenofovir DF is 9-[(R)-2-[[Bis[[(isopropoxycarbonyl)oxy]methoxy]phosphinyl]methoxy]propyl]adenine fumarate (1:1). It has a molecular formula of C19H30N5O10P•C4H4O4 and a molecular weight of 635.51. It has the following structural formula:

Tenofovir DF is a white to off-white powder with a solubility of 13.4 mg/mL in distilled water at 25°C. It has an octanol/phosphate buffer (pH 6.5) partition coefficient (log p) of 1.25 at 25°C.

CIMDUO tablets are for oral administration. Each film-coated tablet contains 300 mg of lamivudine and 300 mg of tenofovir disoproxil fumarate, which is equivalent to 245 mg of tenofovir disoproxil, and the following inactive ingredients: croscarmellose sodium, lactose monohydrate, magnesium stearate and microcrystalline cellulose. The tablet coating contains polyethylene glycol, titanium dioxide, polyvinyl alcohol and talc.

12 CLINICAL PHARMACOLOGY

12.1 Mechanism of Action

CIMDUO is a fixed-dose combination of antiviral drugs 3TC and TDF with antiviral activity against HIV-1 [see Microbiology (12.4)].

12.3 Pharmacokinetics

Lamivudine

After oral administration of 2 mg/kg of 3TC twice a day to 9 adults with HIV-1, the peak serum 3TC concentration (Cmax) was 1.5 ± 0.5 mcg/mL (mean ± SD). The area under the plasma concentration versus time curve (AUC) and Cmax increased in proportion to oral dose over the range from 0.25 to 10 mg/kg and absolute bioavailability in 12 adult patients was 86% ± 16% (mean ± SD) for the 150-mg tablet and 87% ± 13% for the oral solution. Binding of 3TC to human plasma proteins is low (< 36%). Within 12 hours after a single oral dose of 3TC in 6 HIV-1-infected adults, 5.2% ± 1.4% (mean ± SD) of the dose was excreted as the trans-sulfoxide metabolite in the urine. The majority of 3TC is eliminated unchanged in urine by active organic cationic secretion and the observed mean elimination half-life (t1/2) ranged from 5 to 7 hours in most single-dose studies with serum sampling for 24 hours after dosing.

Tenofovir Disoproxil Fumarate

Following oral administration of a single 300-mg dose of TDF to HIV-1-infected subjects in the fasted state, maximum serum concentrations (Cmax) were achieved in 1.0 ± 0.4 hrs (mean ± SD) and Cmax and AUC values were 296 ± 90 ng/mL and 2287 ± 685 ng•hr/mL, respectively. The oral bioavailability of tenofovir from TDF in fasted subjects is approximately 25%. Less than 0.7% of tenofovir binds to human plasma proteins in vitro and the binding is independent of concentration over the range of 0.01 to 25 mcg/mL. Approximately 70 to 80% of the intravenous dose of tenofovir is recovered as unchanged drug in the urine. Tenofovir is eliminated by a combination of glomerular filtration and active tubular secretion with a renal clearance in adults with normal renal function of 243 ± 33 mL/min (mean ± SD). Following a single oral dose, the terminal elimination half-life of tenofovir is approximately 17 hours.

Special Populations

Race

Lamivudine

There are no significant or clinically relevant racial differences in lamivudine pharmacokinetics.

Tenofovir Disoproxil Fumarate

There were insufficient numbers from racial and ethnic groups other than Caucasian to adequately determine potential pharmacokinetic differences among these populations.

Gender

There are no significant or clinically relevant gender differences in the pharmacokinetics of lamivudine and tenofovir.

Geriatric Patients

The pharmacokinetics of lamivudine and tenofovir have not been studied in patients over 65 years of age.

Patients with Renal Impairment

[See Use in Specific Populations (8.6).]

Lamivudine

The pharmacokinetics of lamivudine are altered in subjects with renal impairment (Table 3).

Table 3. Pharmacokinetic Parameters (Mean ± SD) After a Single 300-mg Oral Dose of 3TC in Subjects with Varying Degrees of Renal Function
Parameter | Creatinine Clearance Criterion (Number of Subjects)
Parameter | > 60 mL/min; (n = 6) | 10-30 mL/min; (n = 4) | < 10 mL/min; (n = 6)
Creatinine clearance (mL/min) | 111 ± 14 | 28 ± 8 | 6 ± 2
Cmax (mcg/mL) | 2.6 ± 0.5 | 3.6 ± 0.8 | 5.8 ± 1.2
AUC∞ (mcg•h/mL) | 11.0 ± 1.7 | 48.0 ± 19 | 157 ± 74
Cl/F (mL/min) | 464 ± 76 | 114 ± 34 | 36 ± 11

Tenofovir Disoproxil Fumarate

The pharmacokinetics of tenofovir are altered in subjects with renal impairment [see Warnings and Precautions (5.3)]. In subjects with creatinine clearance below 50 mL/min or with end‑stage renal disease (ESRD) requiring dialysis, Cmax, and AUC0‑∞ of tenofovir were increased.

Table 4. Pharmacokinetic Parameters (Mean ± SD) of Tenofovir in Subjects After a Single 300-mg Oral Dose of TDF in Subjects with Varying Degrees of Renal Function
Baseline Creatinine Clearance (mL/min) | > 80; (N = 3) | 50-80; (N = 10) | 30-49; (N = 8) | 12-29; (N = 11)
Cmax (µg/mL) | 0.34 ± 0.03 | 0.33 ± 0.06 | 0.37 ± 0.16 | 0.60 ± 0.19
AUC0-∞ (µg•hr/mL) | 2.18 ± 0.26 | 3.06 ± 0.93 | 6.01 ± 2.50 | 15.98 ± 7.22
CL/F (mL/min) | 1043.7 ± 115.4 | 807.7 ± 279.2 | 444.4 ± 209.8 | 177.0 ± 97.1
CLrenal (mL/min) | 243.5 ± 33.3 | 168.6 ± 27.5 | 100.6 ± 27.5 | 43.0 ± 31.2

Patients with Hepatic Impairment:

Lamivudine

The pharmacokinetics of lamivudine were not altered by diminishing hepatic function. Safety and efficacy of lamivudine have not been established in the presence of decompensated liver disease.

Tenofovir Disoproxil Fumarate

The pharmacokinetics of tenofovir following a 300 mg single dose of TDF have been studied in non-HIV-infected subjects with moderate to severe (Child-Pugh B to C) hepatic impairment. There were no substantial alterations in tenofovir pharmacokinetics in subjects with hepatic impairment compared with unimpaired subjects.

Assessment of Drug Interactions

[See Drug Interactions (7).]

Lamivudine

Effect of 3TC on the Pharmacokinetics of Other Agents

Based on in vitro study results, 3TC at therapeutic drug exposures is not expected to affect the pharmacokinetics of drugs that are substrates of the following transporters: organic anion transporter polypeptide 1B1/3 (OATP1B1/3), breast cancer resistance protein (BCRP), P-glycoprotein (P-gp), multidrug and toxin extrusion protein 1 (MATE1), MATE2-K, organic cation transporter 1 (OCT1), OCT2, or OCT3.

Effect of Other Agents on the Pharmacokinetics of 3TC

3TC is a substrate of MATE1, MATE2-K, and OCT2 in vitro. Trimethoprim (an inhibitor of these drug transporters) has been shown to increase 3TC plasma concentrations. This interaction is not considered clinically significant as no dose adjustment of 3TC is needed.

3TC is a substrate of P-gp and BCRP; however, considering its absolute bioavailability (87%), it is unlikely that these transporters play a significant role in the absorption of 3TC. Therefore, coadministration of drugs that are inhibitors of these efflux transporters is unlikely to affect the disposition and elimination of 3TC.

Interferon Alfa

There was no significant pharmacokinetic interaction between 3TC and interferon alfa in a trial of 19 healthy male subjects [see Warnings and Precautions (5.4)].

Ribavirin

In vitro data indicate ribavirin reduces phosphorylation of 3TC, stavudine, and zidovudine. However, no pharmacokinetic (e.g., plasma concentrations or intracellular triphosphorylated active metabolite concentrations) or pharmacodynamic (e.g., loss of HIV-1/HCV virologic suppression) interaction was observed when ribavirin and 3TC (n = 18), stavudine (n = 10), or zidovudine (n = 6) were coadministered as part of a multi-drug regimen to HIV-1/HCV co-infected subjects [see Warnings and Precautions (5.4)].

Sorbitol (Excipient)

3TC and sorbitol solutions were coadministered to 16 healthy adult subjects in an open-label, randomized sequence, 4-period, crossover trial. Each subject received a single 300-mg dose of 3TC oral solution alone or coadministered with a single dose of 3.2 grams, 10.2 grams, or 13.4 grams of sorbitol in solution. Coadministration of 3TC with sorbitol resulted in dose-dependent decreases of 20%, 39%, and 44% in the AUC(0-24), 14%, 32%, and 36% in the AUC(∞), and 28%, 52%, and 55% in the Cmax of lamivudine.

Trimethoprim/Sulfamethoxazole

3TC and TMP/SMX were coadministered to 14 HIV-1-positive subjects in a single-center, open-label, randomized, crossover trial. Each subject received treatment with a single 300-mg dose of 3TC and TMP 160 mg/SMX 800 mg once a day for 5 days with concomitant administration of 3TC 300 mg with the fifth dose in a crossover design. Coadministration of TMP/SMX with 3TC resulted in an increase of 43% ± 23% (mean ± SD) in 3TC AUC∞, a decrease of 29% ± 13% in 3TC oral clearance, and a decrease of 30% ± 36% in 3TC renal clearance. The pharmacokinetic properties of TMP and SMX were not altered by coadministration with 3TC. There is no information regarding the effect on 3TC pharmacokinetics of higher doses of TMP/SMX such as those used in treating PCP.

Tenofovir Disoproxil Fumarate

At concentrations substantially higher (~300-fold) than those observed in vivo, tenofovir did not inhibit in vitro CYP3A4, CYP2D6, CYP2C9, or CYP2E1. However, a small (6%) but statistically significant reduction in metabolism of CYP1A substrate was observed. Based on the results of in vitro experiments and the known elimination pathway of tenofovir, the potential for CYP mediated interactions involving TDF with other medicinal products is low.

TDF has been evaluated in healthy volunteers in combination with other antiretroviral and potential concomitant drugs. Tables 5 and 6 summarize pharmacokinetic effects of coadministered drug on tenofovir pharmacokinetics and effects of TDF on the pharmacokinetics of coadministered drug. Coadministration of TDF with didanosine results in changes in the pharmacokinetics of didanosine that may be of clinical significance. Concomitant dosing of TDF with didanosine significantly increases the Cmax and AUC of didanosine. When didanosine 250 mg enteric-coated capsules were administered with TDF, systemic exposures of didanosine were similar to those seen with the 400 mg enteric-coated capsules alone under fasted conditions (Table 5). The mechanism of this interaction is unknown.

No clinically significant drug interactions have been observed between TDF and efavirenz, methadone, nelfinavir, oral contraceptives, ribavirin, or sofosbuvir.

Table 5. Drug Interactions: Changes in Pharmacokinetic Parameters for Tenofovir [Subjects received TDF 300 mg once daily.] in the Presence of the Coadministered Drug
Coadministered Drug | Dose of Coadministered Drug (mg) | % Change of Tenofovir Pharmacokinetic Parameters [Increase = ↑; Decrease = ↓; No Effect = ↔]; (90% CI)
Coadministered Drug | Dose of Coadministered Drug (mg) | Cmax | AUC | Cmin
Atazanavir [Reyataz® (atazanavir) Prescribing Information.] | 400 once daily × 14 days | ↑ 14; (↑ 8 to ↑ 20) | ↑ 24; (↑ 21 to ↑ 28) | ↑ 22; (↑ 15 to ↑ 30)
Atazanavir/; Ritonavir [Prezista® (darunavir) Prescribing Information.] | 300/100 once daily | ↑ 34; (↑ 20 to ↑ 51) | ↑ 37; (↑ 30 to ↑ 45) | ↑ 29; (↑ 21 to ↑ 36)
Darunavir/; Ritonavir | 300/100 twice daily | ↑ 24; (↑ 8 to ↑ 42) | ↑ 22; (↑ 10 to ↑ 35) | ↑ 37; (↑ 19 to ↑ 57)
Indinavir | 800 three times daily × 7 days | ↑ 14; (↓ 3 to ↑ 33) | ↔ | ↔
Ledipasvir/; Sofosbuvir [Data generated from simultaneous dosing with HARVONI (ledipasvir/sofosbuvir). Staggered administration (12 hours apart) provide similar results.] [Comparison based on exposures when administered as atazanavir/ritonavir + emtricitabine/TDF.] | 90/400 once daily × 10 days | ↑ 47; (↑ 37 to ↑ 58) | ↑ 35; (↑ 29 to ↑ 42) | ↑ 47; (↑ 38 to ↑ 57)
Ledipasvir/; Sofosbuvir [Comparison based on exposures when administered as darunavir/ritonavir + emtricitabine/TDF.] | 90/400 once daily × 10 days | ↑ 64; (↑ 54 to ↑ 74) | ↑ 50; (↑ 42 to ↑ 59) | ↑ 59; (↑ 49 to ↑ 70)
Ledipasvir/; Sofosbuvir [Study conducted with ATRIPLA® (efavirenz/emtricitabine/tenofovir DF) coadministered with HARVONI.] | 90/400 once daily × 14 days | ↑ 79; (↑ 56 to ↑ 104) | ↑ 98; (↑ 77 to ↑ 123) | ↑ 163; (↑ 132 to ↑ 197)
Ledipasvir/; Sofosbuvir [Study conducted with COMPLERA® (emtricitabine/rilpivirine/tenofovir DF) coadministered with HARVONI.] | 90/400 once daily × 10 days | ↑ 32; (↑ 25 to ↑ 39) | ↑ 40; (↑ 31 to ↑ 50) | ↑ 91; (↑ 74 to ↑ 110)
Ledipasvir/; Sofosbuvir [Study conducted with TRUVADA® (emtricitabine/tenofovir DF) + dolutegravir coadministered with HARVONI.] | 90/400 once daily × 10 days | ↑ 61; (↑ 51 to ↑ 72) | ↑ 65; (↑ 59 to ↑ 71) | ↑ 115; (↑ 105 to ↑ 126)
Lopinavir/; Ritonavir | 400/100 twice daily × 14 days | ↔ | ↑ 32; (↑ 25 to ↑ 38) | ↑ 51; (↑ 37 to ↑ 66)
Saquinavir/; Ritonavir | 1000/100 twice daily × 14 days | ↔ | ↔ | ↑ 23; (↑ 16 to ↑ 30)
Sofosbuvir [Study conducted with ATRIPLA coadministered with SOVALDI® (sofosbuvir).] | 400 single dose | ↑ 25; ↑ 8 to ↑ 45) | ↔ | ↔
Sofosbuvir/; Velpatasvir [Comparison based on exposures when administered as atazanavir/ritonavir + emtricitabine/tenofovir DF.] | 400/100 once daily | ↑ 55; (↑ 43 to ↑ 68) | ↑ 30; (↑ 24 to ↑ 36) | ↑ 39; (↑ 31 to ↑ 48)
Sofosbuvir/; Velpatasvir [Comparison based on exposures when administered as darunavir/ritonavir + emtricitabine/tenofovir DF.] | 400/100 once daily | ↑ 55; (↑ 45 to ↑ 66) | ↑ 39; (↑ 33 to ↑ 44) | ↑ 52; (↑ 45 to ↑ 59)
Sofosbuvir/; Velpatasvir [Study conducted with ATRIPLA coadministered with EPCLUSA (sofosbuvir/velpatasvir).] | 400/100 once daily | ↑ 77; (↑ 53 to ↑ 104) | ↑ 81; (↑ 68 to ↑ 94) | ↑ 121; (↑ 100 to ↑ 143)
Sofosbuvir/; Velpatasvir [Study conducted with STRIBILD® (elvitegravir/cobicistat/emtricitabine/tenofovir DF) coadministered with EPCLUSA.] | 400/100 once daily | ↑ 36; (↑ 25 to ↑ 47) | ↑ 35; (↑ 29 to ↑ 42) | ↑ 45; (↑ 39 to ↑ 51)
Sofosbuvir/; Velpatasvir [Study conducted with COMPLERA coadministered with EPCLUSA.] | 400/100 once daily | ↑ 44; (↑ 33 to ↑ 55) | ↑ 40; (↑ 34 to ↑ 46) | ↑ 84; (↑ 76 to ↑ 92)
Sofosbuvir/; Velpatasvir [Administered as raltegravir + emtricitabine/tenofovir DF.] | 400/100 once daily | ↑ 46; (↑ 39 to ↑ 54) | ↑ 40; (↑ 34 to ↑ 45) | ↑ 70; (↑ 61 to ↑ 79)
Tacrolimus | 0.05 mg/kg twice daily × 7 days | ↑ 13; (↑ 1 to ↑ 27) | ↔ | ↔
Tipranavir/; Ritonavir [Aptivus® (tipranavir) Prescribing Information.] | 500/100 twice daily | ↓ 23; (↓ 32 to ↓ 13) | ↓ 2; (↓ 9 to ↑ 5) | ↑ 7; (↓ 2 to ↑ 17)
Tipranavir/; Ritonavir [Aptivus® (tipranavir) Prescribing Information.] | 750/200 twice daily (23 doses) | ↓ 38; (↓ 46 to ↓ 29) | ↑ 2; (↓ 6 to ↑ 10) | ↑ 14; (↑ 1 to ↑ 27)

No effect on the pharmacokinetic parameters of the following coadministered drugs was observed with TDF: abacavir, didanosine (buffered tablets), emtricitabine, entecavir, and lamivudine.

Table 6. Drug Interactions: Changes in Pharmacokinetic Parameters for Coadministered Drug in the Presence of TDF
Coadministered Drug | Dose of Coadministered Drug (mg) | % Change of Coadministered Drug Pharmacokinetic Parameters [Increase = ↑; Decrease = ↓; No Effect = ↔; NA = Not Applicable]; (90% CI)
Coadministered Drug | Dose of Coadministered Drug (mg) | Cmax | AUC | Cmin
Abacavir | 300 once | ↑ 12; (↓ 1 to ↑ 26) | ↔ | NA
Atazanavir [Reyataz (atazanavir) Prescribing Information.] | 400 once daily × 14 days | ↓ 21; (↓ 27 to ↓ 14) | ↓ 25; (↓ 30 to ↓ 19) | ↓ 40; (↓ 48 to ↓ 32)
Atazanavir | Atazanavir/; Ritonavir 300/100 once daily × 42 days | ↓ 28; (↓ 50 to ↑ 5) | ↓ 25 [In HIV-infected subjects, addition of TDF to atazanavir 300 mg plus ritonavir 100 mg, resulted in AUC and Cmin values of atazanavir that were 2.3- and 4-fold higher than the respective values observed for atazanavir 400 mg when given alone.]; (↓ 42 to ↓ 3) | ↓ 23; (↓ 46 to ↑ 10)
Darunavir [Prezista (darunavir) Prescribing Information.] | Darunavir/Ritonavir 300/100 once daily | ↑ 16; (↓ 6 to ↑ 42) | ↑ 21; (↓ 5 to ↑ 54) | ↑ 24; (↓ 10 to ↑ 69)
Didanosine [Videx® EC Prescribing Information. Subjects received didanosine enteric-coated capsules.] | 250 once, simultaneously with VIREAD® and a light meal [373 kcal, 8.2 g fat] | ↓ 20 [Compared with didanosine (enteric-coated) 400 mg administered alone under fasting conditions.]; (↓ 32 to ↓ 7) | ↔ | NA
Emtricitabine | 200 once daily × 7 days | ↔ | ↔ | ↑ 20; (↑ 12 to ↑ 29)
Entecavir | 1 mg once daily × 10 days | ↔ | ↑ 13; (↑ 11 to ↑ 15) | ↔
Indinavir | 800 three times daily × 7 days | ↓ 11; (↓ 30 to ↑ 12) | ↔ | ↔
Lamivudine | 150 twice daily × 7 days | ↓ 24; (↓ 34 to ↓ 12) | ↔ | ↔
Lopinavir; Ritonavir | Lopinavir/Ritonavir 400/100 twice daily × 14 days | ↔ ↔ | ↔; ↔ | ↔; ↔
Saquinavir | Saquinavir/Ritonavir 1000/100 twice daily × 14 days | ↑ 22; (↑ 6 to ↑ 41) | ↑ 29 [Increases in AUC and Cmin are not expected to be clinically relevant; hence no dose adjustments are required when tenofovir DF and ritonavir-boosted saquinavir are coadministered.]; (↑ 12 to ↑ 48) | ↑ 47; (↑ 23 to ↑ 76)
Ritonavir | Saquinavir/Ritonavir 1000/100 twice daily × 14 days | ↔ | ↔ | ↑ 23; (↑ 3 to ↑ 46)
Tacrolimus | 0.05 mg/kg twice daily × 7 days | ↔ | ↔ | ↔
Tipranavir [Aptivus (tipranavir) Prescribing Information.] | Tipranavir/Ritonavir 500/100 twice daily | ↓ 17; (↓ 26 to ↓ 6) | ↓ 18; (↓ 25 to ↓ 9) | ↓ 21; (↓ 30 to ↓ 10)
Tipranavir [Aptivus (tipranavir) Prescribing Information.] | Tipranavir/Ritonavir 750/200 twice daily (23 doses) | ↓ 11; (↓ 16 to ↓ 4) | ↓ 9; (↓ 15 to ↓ 3) | ↓ 12; (↓ 22 to 0)

12.4 Microbiology

Mechanism of Action

Lamivudine

3TC is a synthetic nucleoside analogue with activity against HIV-1 and HBV. Intracellularly, 3TC is phosphorylated to its active 5’‑triphosphate metabolite, lamivudine triphosphate (3TC-TP). The principal mode of action of 3TC‑TP is inhibition of HIV-1 reverse transcriptase (RT) via DNA chain termination after incorporation of the nucleotide analogue.

Tenofovir Disoproxil Fumarate

TDF is an acyclic nucleoside phosphonate diester analog of adenosine monophosphate. TDF requires initial diester hydrolysis for conversion to tenofovir and subsequent phosphorylations by cellular enzymes to form tenofovir diphosphate. Tenofovir diphosphate inhibits the activity of HIV-1 reverse transcriptase and HBV reverse transcriptase by competing with the natural substrate deoxyadenosine 5’-triphosphate and, after incorporation into DNA, by DNA chain termination. Tenofovir diphosphate is a weak inhibitor of mammalian DNA polymerases α, β, and mitochondrial DNA polymerase γ.

Antiviral Activity

Lamivudine

The antiviral activity of 3TC against HIV-1 was assessed in a number of cell lines (including monocytes and fresh human peripheral blood lymphocytes (PBMCs) using standard susceptibility assays. EC50 values were in the range of 3 to 15,000 nM. (1 μM = 0.23 mcg/mL). The median EC50 values of 3TC were 60 nM (range: 20 to 70 nM), 35 nM (range: 30 to 40 nM), 30 nM (range: 20 to 90 nM), 20 nM (range: 3 to 40 nM), 30 nM (range: 1 to 60 nM), 30 nM (range: 20 to 70 nM), 30 nM (range: 3 to 70 nM), and 30 nM (range: 20 to 90 nM) against HIV-1 clades A-G and group O viruses (n = 3 except n = 2 for clade B), respectively. The EC50 values against HIV-2 isolates (n = 4) ranged from 3 to 120 nM in PBMCs. 3TC was not antagonistic to all tested anti-HIV agents. Ribavirin (50 μM) used in the treatment of chronic HCV infection decreased the anti-HIV-1 activity of 3TC by 3.5-fold in MT-4 cells.

Tenofovir Disoproxil Fumarate

The antiviral activity of tenofovir against laboratory and clinical isolates of HIV-1 was assessed in lymphoblastoid cell lines, primary monocyte/macrophage cells and peripheral blood lymphocytes. The EC50 (50% effective concentration) values for tenofovir were in the range of 0.04 μM to 8.5 μM. Tenofovir displayed antiviral activity in cell culture against HIV-1 clades A, B, C, D, E, F, G, and O (EC50 values ranged from 0.5 μM to 2.2 μM) and strain-specific activity against HIV-2 (EC50 values ranged from 1.6 μM to 5.5 μM). Please see the full prescribing information for VIREAD for information regarding the inhibitory activity of TDF against HBV.

Resistance

Lamivudine

3TC-resistant variants of HIV‑1 have been selected in cell culture. Genotypic analysis showed that resistance was predominantly due to a methionine to valine or isoleucine (M184V/I) substitution in reverse transcriptase.

Tenofovir Disoproxil Fumarate

HIV-1 isolates with reduced susceptibility to tenofovir have been selected in cell culture. These viruses expressed a K65R substitution in reverse transcriptase and showed a 2- to 4-fold reduction in susceptibility to tenofovir. In addition, a K70E substitution in HIV-1 reverse transcriptase has been selected by tenofovir and results in low-level reduced susceptibility to tenofovir. K65R substitutions developed in some subjects failing a tenofovir disoproxil fumarate regimen.

Cross-Resistance

Lamivudine

Cross-resistance among NRTIs has been observed. 3TC-resistant HIV-1 isolates were cross-resistant in cell culture to didanosine (ddI). Cross-resistance is also expected with abacavir and emtricitabine as these select M184V substitutions.

Tenofovir Disoproxil Fumarate

Cross-resistance among NRTIs has been observed. The K65R and K70E substitutions selected by tenofovir are also selected in some HIV-1-infected subjects treated with abacavir or didanosine. HIV-1 isolates with the K65R substitution also showed reduced susceptibility to FTC and 3TC. HIV-1 isolates from subjects (N = 20) whose HIV-1 expressed a mean of 3 zidovudine-associated RT amino acid substitutions (M41L, D67N, K70R, L210W, T215Y/F, or K219Q/E/N) showed a 3.1-fold decrease in the susceptibility to tenofovir. Subjects whose virus expressed an L74V substitution without zidovudine resistance-associated substitutions (N = 8) had reduced response to VIREAD. Limited data are available for patients whose virus expressed a Y115F substitution (N = 3), Q151M substitution (N = 2), or T69 insertion (N = 4), all of whom had a reduced response.

13 NONCLINICAL TOXICOLOGY

13.1 Carcinogenesis, Mutagenesis, Impairment of Fertility

Lamivudine

Long-term carcinogenicity studies with 3TC in mice and rats showed no evidence of carcinogenic potential at exposures up to 10 times (mice) and 58 times (rats) the human exposures at the recommended dose of 300 mg. 3TC was not mutagenic in a microbial mutagenicity assay, in an in vitro cell transformation assay, in a rat micronucleus test, in a rat bone marrow cytogenetic assay, and in assay for unscheduled DNA synthesis in rat liver. 3TC showed no evidence of in vivo genotoxic activity in the rat at oral doses of up to 2000 mg per kg, producing plasma levels of 35 to 45 times those in humans at the recommended dose for HIV‑1 infection. In a study of reproductive performance, 3TC administered to rats at doses up to 4,000 mg per kg per day, producing plasma levels 47 to 70 times those in humans, revealed no evidence of impaired fertility and no effect on the survival, growth, and development to weaning of the offspring.

Tenofovir Disoproxil Fumarate

Long-term oral carcinogenicity studies of TDF in mice and rats were carried out at exposures up to approximately 16 times (mice) and 5 times (rats) those observed in humans at the therapeutic dose for HIV-1 infection. At the high dose in female mice, liver adenomas were increased at exposures 16 times that in humans. In rats, the study was negative for carcinogenic findings at exposures up to 5 times that observed in humans at the therapeutic dose.

TDF was mutagenic in the in vitro mouse lymphoma assay and negative in an in vitro bacterial mutagenicity test (Ames test). In an in vivo mouse micronucleus assay, TDF was negative when administered to male mice.

There were no effects on fertility, mating performance or early embryonic development when TDF was administered to male rats at a dose equivalent to 10 times the human dose based on body surface area comparisons for 28 days prior to mating and to female rats for 15 days prior to mating through day seven of gestation. There was, however, an alteration of the estrous cycle in female rats.

13.2 Animal Toxicology and/or Pharmacology

Tenofovir Disoproxil Fumarate

Tenofovir and TDF administered in toxicology studies to rats, dogs, and monkeys at exposures (based on AUCs) greater than or equal to 6-fold those observed in humans caused bone toxicity. In monkeys the bone toxicity was diagnosed as osteomalacia. Osteomalacia observed in monkeys appeared to be reversible upon dose reduction or discontinuation of tenofovir. In rats and dogs, the bone toxicity manifested as reduced bone mineral density. The mechanism(s) underlying bone toxicity is unknown.

Evidence of renal toxicity was noted in 4 animal species. Increases in serum creatinine, BUN, glycosuria, proteinuria, phosphaturia, and/or calciuria and decreases in serum phosphate were observed to varying degrees in these animals. These toxicities were noted at exposures (based on AUCs) 2 to 20 times higher than those observed in humans. The relationship of the renal abnormalities, particularly the phosphaturia, to the bone toxicity is not known.

14 CLINICAL STUDIES

14.1 Clinical Efficacy in Patients with HIV-1 Infection

Treatment-Naïve Adult Patients

Trial 903

Data through 144 weeks are reported for Trial 903, a double-blind, active-controlled multicenter trial comparing EFV 600 mg + 3TC 300 mg + TDF 300 mg vs. EFV 600 mg + 3TC 300 mg + stavudine (d4T) 40 mg in 600 antiretroviral-naïve subjects. Subjects had a mean age of 36 years (range 18-64); 74% were male, 64% were Caucasian, and 20% were Black. The mean baseline CD4+ cell count was 279 cells/mm^3 (range 3-956) and median baseline plasma HIV-1 RNA was 77,600 copies/mL (range 417-5,130,000). Subjects were stratified by baseline HIV-1 RNA and CD4+ cell count. Forty-three percent of subjects had baseline viral loads > 100,000 copies/mL and 39% had CD4+ cell counts < 200 cells/mm^3. Treatment outcomes through 48 and 144 weeks are presented in Table 7.

Table 7. Outcomes of Randomized Treatment at Week 48 and 144 (Study 903)
Outcomes | At Week 48 |  | At Week 144
Outcomes | EFV + 3TC + TDF; (N = 299) | EFV + 3TC + d4T; (N = 301) | EFV + 3TC + TDF; (N = 299) | EFV + 3TC + d4T; (N = 301)
Responder [Subjects achieved and maintained confirmed HIV-1 RNA < 400 copies/mL through Week 48 and 144.] | 79% | 82% | 68% | 62%
Virologic failure [Includes confirmed viral rebound and failure to achieve confirmed < 400 copies/mL through Week 48 and 144.] | 6% | 4% | 10% | 8%
Rebound | 5% | 3% | 8% | 7%
Never suppressed | 0% | 1% | 0% | 0%
Added an antiretroviral agent | 1% | 1% | 2% | 1%
Death | < 1% | 1% | < 1% | 2%
Discontinued due to adverse event | 6% | 6% | 8% | 13%
Discontinued for other reasons [Includes lost to follow-up, subject’s withdrawal, noncompliance, protocol violation and other reasons.] | 8% | 7% | 14% | 15%

Achievement of plasma HIV-1 RNA concentrations of less than 400 copies/mL at Week 144 was similar between the two treatment groups for the population stratified at baseline on the basis of HIV-1 RNA concentration (> or ≤ 100,000 copies/mL) and CD4+ cell count (< or ≥ 200 cells/mm^3). Through 144 weeks of therapy, 62% and 58% of subjects in the TDF and stavudine arms, respectively, achieved and maintained confirmed HIV-1 RNA < 50 copies/mL. The mean increase from baseline in CD4+ cell count was 263 cells/mm^3 for the TDF arm and 283 cells/mm^3 for the stavudine arm.

Through 144 weeks, 11 subjects in the TDF group and 9 subjects in the stavudine group experienced a new CDC Class C event.

16 HOW SUPPLIED/STORAGE AND HANDLING

CIMDUO (lamivudine and tenofovir disoproxil fumarate) tablets 300 mg/300 mg are white to off-white, film-coated, oval tablets debossed with “M112” on one side and plain on the other side.

They are supplied as follows:

NDC 49502-450-93
cartons containing bottles of 30 tablets with desiccant, induction seal and child-resistant cap

NDC 49502-450-77
cartons containing bottles of 90 tablets with desiccant, induction seal and child-resistant cap

Store at 20°C to 25°C (68°F to 77°F); excursions permitted to 15°C to 30°C (59°F to 86°F). [See USP Controlled Room Temperature.]

Dispense in original container.

17 PATIENT COUNSELING INFORMATION

Advise the patient to read the FDA-approved patient labeling (Patient Information).

Lactic Acidosis and Severe Hepatomegaly: Inform patients that lactic acidosis and severe hepatomegaly with steatosis, including fatal cases, have been reported. Treatment with CIMDUO should be suspended in any patient who develops clinical symptoms suggestive of lactic acidosis or pronounced hepatotoxicity (including nausea, vomiting, unusual or unexpected stomach discomfort, and weakness) [see Warnings and Precautions (5.1)].

Post Treatment Acute Exacerbation of Hepatitis B in Patients with HBV Co-Infection: Severe acute exacerbations of hepatitis have been reported in patients who are infected with HBV or coinfected with HBV and HIV-1 and have discontinued 3TC and TDF, components of CIMDUO. Test patients with HIV-1 for hepatitis B virus (HBV) before initiating antiretroviral therapy. In patients with chronic hepatitis B, it is important to obtain HIV antibody testing prior to initiating 3TC and TDF, components of CIMDUO [see Warnings and Precautions (5.2)].

New Onset or Worsening Renal Impairment: Inform patients that renal impairment, including cases of acute renal failure and Fanconi syndrome, has been reported. Advise patients with impaired renal function (i.e., creatinine clearance less than 50 mL/min) or patients with end-stage renal disease (ESRD) requiring hemodialysis to avoid CIMDUO with concurrent or recent use of a nephrotoxic agent (e.g., high-dose or multiple NSAIDs) for patients [see Dosage and Administration (2.3), Warnings and Precautions (5.3)].

Risk of Hepatic Decompensation in Patients with HIV-1/HCV Co-Infection: Inform patients with HIV-1/HCV co-infection that hepatic decompensation (some fatal) has occurred in HIV-1/HCV co-infected patients receiving combination antiretroviral therapy for HIV-1 and interferon alfa with or without ribavirin [see Warnings and Precautions (5.4)].

Pancreatitis: Advise patients or guardians to monitor pediatric patients for signs and symptoms of pancreatitis [see Warnings and Precautions (5.5)].

Decreases in Bone Mineral Density: Advise patients that decreases in bone mineral density have been observed with the use of 3TC and TDF, components of CIMDUO, in patients with HIV [see Warnings and Precautions (5.6)].

Immune Reconstitution Syndrome: Advise patients to inform their healthcare provider immediately of any symptoms of infection, as in some patients with advanced HIV infection, signs and symptoms of inflammation from previous infections may occur soon after anti-HIV treatment is started [see Warnings and Precautions (5.7)].

Fat Redistribution: Inform patients that redistribution or accumulation of body fat may occur in patients receiving antiretroviral therapy, including CIMDUO, and that the cause and long‑term health effects of these conditions are not known at this time [see Warnings and Precautions (5.8)].

Administration Instructions: Inform patients that it is important to take CIMDUO once daily on a regular dosing schedule and to avoid missing doses as it can result in development of resistance. Advise patients if a dose is missed, take it as soon as possible unless it is almost time for the next dose [see Dosage and Administration (2.2)].

Pregnancy Registry: Advise patients that there is an antiretroviral pregnancy registry to monitor fetal outcomes in women exposed to CIMDUO [see Use in Specific Populations (8.1)].

Lactation: Instruct women with HIV-1 infection not to breastfeed because HIV-1 can be passed to the baby in breast milk [see Use in Specific Populations (8.2)].

Rx only

Manufactured for:
Mylan Specialty L.P.
Morgantown, WV 26505 U.S.A.

Manufactured by:
Mylan Laboratories Limited
Hyderabad — 500 096, India

© 2021 Viatris Inc.

CIMDUO is a registered trademark of Mylan Pharmaceuticals Inc., a Viatris Company.

Other brands listed are the registered trademarks of their respective owners and are not trademarks of Mylan Laboratories Limited or Mylan Pharmaceuticals Inc.

Patient Information

CIMDUO® (sim-DEW-oh)
(lamivudine and tenofovir disoproxil fumarate)
tablets

What is the most important information I should know about CIMDUO?

CIMDUO can cause serious side effects, including:

- Too much lactic acid in your blood (lactic acidosis). Lactic acidosis is a serious medical emergency that can lead to death.
  Tell your healthcare provider right away if you get any of the following symptoms that could be signs of lactic acidosis:

- feel very weak or tired
- unusual (not normal) muscle pain
- trouble breathing
- stomach pain with nausea or vomiting

- feel cold, especially in your arms and legs
- feel dizzy or lightheaded
- have a fast or irregular heartbeat

- Severe liver problems. In some cases, severe liver problems can lead to death. Your liver may become large (hepatomegaly) and you may develop fat in your liver (steatosis).
  Call your healthcare provider right away if you get any of the following signs or symptoms of liver problems:

- your skin or the white part of your eyes turns yellow (jaundice)
- dark or “tea-colored” urine
- light-colored stools (bowel movements)

- loss of appetite for several days or longer
- nausea and vomiting
- pain, aching, or tenderness on the right side of your stomach-area

- Worsening of hepatitis B infection. If you have Human Immunodeficiency Virus type 1 (HIV-1) and hepatitis B Virus (HBV) infection, your HBV may get worse (flare-up) if you stop taking CIMDUO. A “flare-up” is when your HBV infection suddenly returns in a worse way than before. Your healthcare provider will test you for HBV infection before you start treatment with CIMDUO.
  - It is not known if CIMDUO is safe and effective in people who have both HIV-1 and HBV infection.
  - Do not run out of CIMDUO. Refill your prescription or talk to your healthcare provider before your CIMDUO is all gone.
  - Do not stop CIMDUO without first talking to your healthcare provider. If you stop taking CIMDUO, your healthcare provider will need to check your health often and do blood tests regularly for several months to check your liver.
- New or worse kidney problems, including kidney failure. Your healthcare provider may do blood and urine tests to check your kidneys before and during treatment with CIMDUO. Tell your healthcare provider if you get signs and symptoms of kidney problems, including bone pain that does not go away or worsening bone pain, pain in your arms, hands, legs or feet, broken (fractured) bones, muscle pain or weakness.

For more information about side effects, see “What are the possible side effects of CIMDUO?”

What is CIMDUO?

CIMDUO is a prescription medicine that is used with other antiretroviral medicines to treat Human Immunodeficiency Virus-1 (HIV-1) in adults and children weighing at least 35 kg.

HIV-1 is the virus that causes AIDS (Acquired Immune Deficiency Syndrome).

CIMDUO contains the prescription medicines lamivudine and tenofovir disoproxil fumarate.

Do not take CIMDUO if you:

- are allergic to lamivudine, tenofovir disoproxil fumarate, or any of the ingredients in CIMDUO. See the end of this Patient Information leaflet for a complete list of ingredients in CIMDUO.

Before you take CIMDUO, tell your healthcare provider about all of your medical conditions, including if you:

- have liver problems, including hepatitis B or C infection
- have kidney problems, including end-stage renal disease (ESRD) that requires dialysis
- have bone problems, including a history of bone fractures
- are pregnant or plan to become pregnant. It is not known if CIMDUO will harm your unborn baby. There is a pregnancy registry for women who take CIMDUO during pregnancy. The purpose of this registry is to collect information about the health of you and your baby. Talk to your healthcare provider about how you can take part in this registry.
- are breastfeeding or plan to breastfeed. Do not breastfeed if you take CIMDUO.
  - You should not breastfeed if you have HIV-1 because of the risk of passing HIV-1 to your baby.
  - Talk to your healthcare provider about the best way to feed your baby.

Tell your healthcare provider about all the medicines you take, including prescription and over-the-counter medicines, vitamins and herbal supplements.

Some medicines interact with CIMDUO. CIMDUO may affect the way other medicines work, and other medicines may affect how CIMDUO works. Keep a list of your medicines and show it to your healthcare provider and pharmacist when you get a new medicine.

- You can ask your healthcare provider or pharmacist for a list of medicines that interact with CIMDUO.
- Do not start taking a new medicine without telling your healthcare provider. Your healthcare provider can tell you if it is safe to take CIMDUO with other medicines.

How should I take CIMDUO?

- Take CIMDUO exactly as your healthcare provider tells you to take it.
- Take CIMDUO 1 time each day with or without food.
- Do not miss a dose of CIMDUO. If you miss a dose, take the missed dose as soon as you remember. If it is almost time for your next dose of CIMDUO, do not take the missed dose. Take the next dose at your regular time.
- Stay under the care of your healthcare provider during treatment with CIMDUO.
- Do not run out of CIMDUO. The virus in your blood may increase and the virus may become harder to treat. When your supply starts to run low, get more from your healthcare provider or pharmacy.
- If you take too much CIMDUO, go to the nearest hospital emergency room right away.

What should I avoid while taking CIMDUO?

You should avoid taking medicines that contain sorbitol during treatment with CIMDUO.

What are the possible side effects of CIMDUO?

CIMDUO may cause serious side effects, including:

- See “What is the most important information I should know about CIMDUO?”
- Use with interferon- and ribavirin-based regimens. Worsening of liver disease that has caused death has happened in people infected with HIV-1 and hepatitis C virus who were taking antiretroviral medicines for HIV-1 and were also being treated for hepatitis C with interferon alfa with or without ribavirin. If you are taking CIMDUO and interferon alfa with or without ribavirin, tell your healthcare provider if you have any new symptoms.
- Risk of inflammation of the pancreas (pancreatitis). Children may be at risk for developing pancreatitis during treatment with CIMDUO if they:
  - have taken nucleoside analogue medicines in the past
  - have a history of pancreatitis
  - have other risk factors for pancreatitis
Call your healthcare provider right away if your child develops signs and symptoms of pancreatitis including severe upper stomach-area pain, with or without nausea and vomiting. Your healthcare provider may tell you to stop giving CIMDUO to your child if their symptoms and blood test results show that your child may have pancreatitis.
- Bone problems can happen in some people who take CIMDUO. Bone problems include bone pain, softening or thinning (which may lead to fractures). Your healthcare provider may need to do tests to check your bones. Tell your healthcare provider if you have any bone pain, pain in your hands or feet, or muscle pain or weakness during treatment with CIMDUO.
- Changes in your immune system (Immune Reconstitution Syndrome) can happen when you start taking HIV-1 medicines. Your immune system may get stronger and begin to fight infections that have been hidden in your body for a long time. Tell your healthcare provider if you start having new symptoms after starting your HIV-1 medicine.
- Changes in body fat can happen in some people who take HIV-1 medicines. These changes may include increased amount of fat in the upper back and neck (“buffalo hump”), breast, and around the main part of your body (trunk). Loss of fat from the legs, arms, and face may also happen. The cause and long-term health effects of these conditions are not known.

The most common side effects of CIMDUO include:

- headache
- pain
- depression

- diarrhea
- rash

Tell your healthcare provider if you have any side effect that bothers you or that does not go away.

These are not all the possible side effects of CIMDUO. Call your doctor for medical advice about side effects. You may report side effects to FDA at 1-800-FDA-1088.

How should I store CIMDUO?

- Store CIMDUO tablets at room temperature between 68°F to 77°F (20°C to 25°C).
- Keep CIMDUO tablets in the original container.

Keep CIMDUO and all medicines out of the reach of children.

General information about the safe and effective use of CIMDUO.

Medicines are sometimes prescribed for purposes other than those listed in a Patient Information leaflet. Do not use CIMDUO for a condition for which it was not prescribed. Do not give CIMDUO to other people, even if they have the same symptoms that you have. It may harm them. If you would like more information, talk with your healthcare provider. You can ask your pharmacist or healthcare provider for information about CIMDUO that is written for health professionals.

What are the ingredients in CIMDUO?

Active ingredient: lamivudine and tenofovir disoproxil fumarate

Inactive ingredients: croscarmellose sodium, lactose monohydrate, magnesium stearate and microcrystalline cellulose. The tablet coating contains polyethylene glycol, titanium dioxide, polyvinyl alcohol and talc.

Manufactured for:
Mylan Specialty L.P.
Morgantown, WV 26505 U.S.A.

Manufactured by:
Mylan Laboratories Limited
Hyderabad — 500 096, India

© 2021 Viatris Inc.

CIMDUO is a registered trademark of Mylan Pharmaceuticals Inc., a Viatris Company.

Other brands listed are the registered trademarks of their respective owners and are not trademarks of Mylan Laboratories Limited or Mylan Pharmaceuticals Inc.

75078442

MS:TLDT:R2

For more information, call Mylan at 1-877-446-3679 (1-877-4-INFO-RX).

This Patient Information has been approved by the U.S. Food and Drug Administration. Revised: 2/2021

PRINCIPAL DISPLAY PANEL – 300 mg/300 mg

NDC 49502-450-93 Rx only

CIMDUO®
(lamivudine and
tenofovir disoproxil
fumarate) tablets
300 mg/300 mg

Each film-coated tablet contains:
Lamivudine, USP 300 mg
Tenofovir Disoproxil
Fumarate 300 mg
equivalent to 245 mg
of tenofovir disoproxil)

Usual Dosage: See accompanying
prescribing information.

Keep this and all medication
out of the reach of children.

Store at 20°C to 25°C (68°F to
77°F). [See USP Controlled Room
Temperature.]

Dispense only in original
container.

Keep container tightly
closed.

Manufactured for:
Mylan Specialty L.P.
Morgantown, WV 26505 U.S.A.

Made in India

Code No.: MH/DRUGS/AD/089

MS:MXA:45093:1C:R2

Mylan.com

© 2021 Viatris Inc.

CIMDUO is a registered
trademark of Mylan
Pharmaceuticals Inc.,
a Viatris Company.